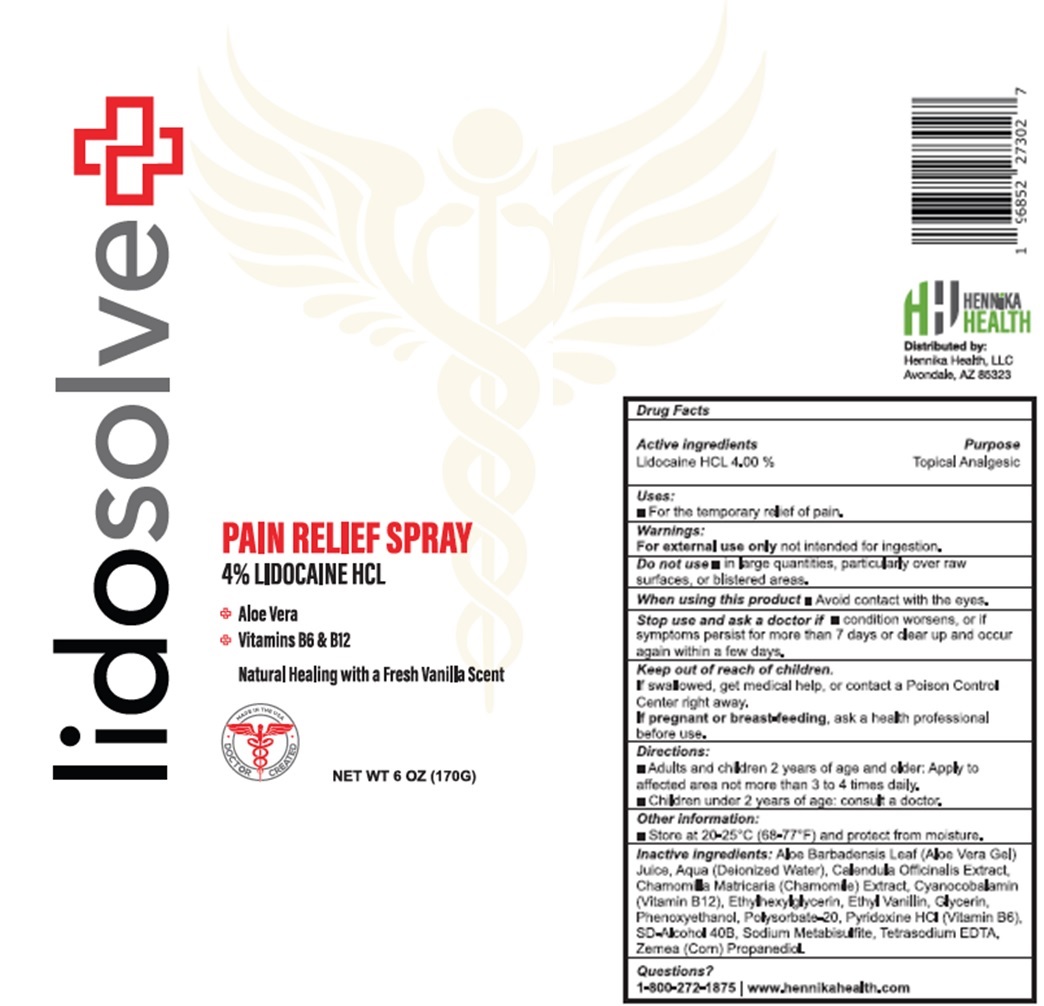 DRUG LABEL: LIDOSOLVE PAIN RELIEF
NDC: 83646-420 | Form: LIQUID
Manufacturer: HENNIKA HEALTH, LLC
Category: otc | Type: HUMAN OTC DRUG LABEL
Date: 20231111

ACTIVE INGREDIENTS: LIDOCAINE HYDROCHLORIDE 40 mg/1 g
INACTIVE INGREDIENTS: ALOE VERA LEAF; WATER; CALENDULA OFFICINALIS FLOWER; CHAMOMILE; CYANOCOBALAMIN; ETHYLHEXYLGLYCERIN; ETHYL VANILLIN; GLYCERIN; PHENOXYETHANOL; POLYSORBATE 20; PYRIDOXINE HYDROCHLORIDE; SODIUM METABISULFITE; EDETATE SODIUM; CORN

LIDOSOLVE PAIN RELIEF SPRAY

Active ingredients

Lidocaine HCL 4.00%

Purpose

Topical Analgesic

Uses:

- For the temporary relief of pain.

Warnings:

not intended for ingestion. For external use only

Do not use

- in large quantities, Particularly over raw surfaces, or blistered areas.

When using this product

- Avoid contact with the eyes.

Stop use and ask a doctor if

- condition worsens, or if symptoms persist for more than 7 days or clear up and occur again within a few days.

Keep out of reach of children.

If swallowed, get medical help, or contact a Poison Control Center right away.

If pregnant or breast-feeding,

ask a health professional before use.

Directions:

- Adults and children 2 years of age and older:Apply to affected area not more than 3 to 4 times daily.
- Children under 2 years of age: consult a doctor.

Other information:

- Store at 20-25°C (68-77°F) and protect from moisture.

Inactive ingredients:

ALoe Barbadensis Leaf (Aloe Vera Gel) JUice, Aqua (Deionized Water), Calendula Officinalis Extract, Chamomilla Matricaria (Chamomile) Extract,Cyanocobalimin (Vitamin B 12), Ethylhexylglycerin, Ethyl Vanillin, Glycerin, Phenoxyethanol, Polysorbate-20, Pyridoxine HCL (Vitamib B6), SD-Alcohol 40B, Sodium Metabisulfite, Tetrasodium EDTA, Zemea (Corn) Propanediol

Questions?

1-800-272-1875 / www.hennikahealth .com